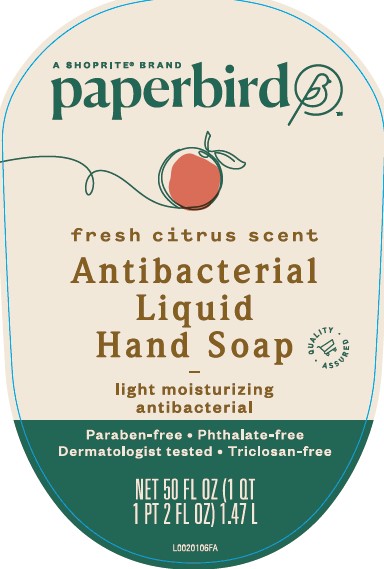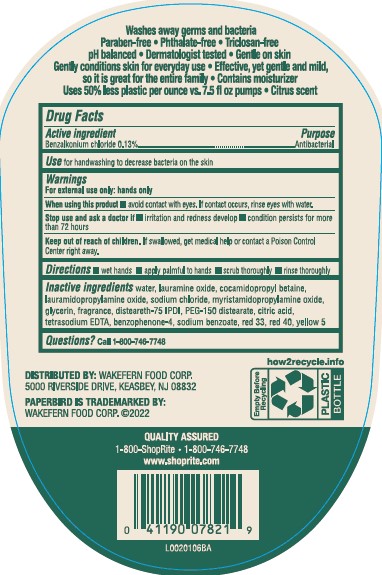 DRUG LABEL: Benzalkonium chloride
NDC: 41190-278 | Form: SOAP
Manufacturer: Wakefern Food Corp.
Category: otc | Type: HUMAN OTC DRUG LABEL
Date: 20260213

ACTIVE INGREDIENTS: BENZALKONIUM CHLORIDE 1.3 g/1 mL
INACTIVE INGREDIENTS: WATER; LAURAMINE OXIDE; COCAMIDOPROPYL BETAINE; LAURAMIDOPROPYLAMINE OXIDE; SODIUM CHLORIDE; MYRISTAMIDOPROPYLAMINE OXIDE; GLYCERIN; DISTEARETH-75 ISOPHORONE DIISOCYANATE; PEG-150 DISTEARATE; CITRIC ACID MONOHYDRATE; EDETATE SODIUM; BENZOPHENONE; SODIUM BENZOATE; FD&C YELLOW NO. 5; FD&C RED NO. 40; D&C RED NO. 33

Paperbird 279.003/279AD
Light Moisturizing Antibacterial Hand Soap

Claims

Washes away germs and bacteria

Paraben-free • Phthalate-free • Triclosan-free

pH balanced • Dermatologist tested • Gentle on skin

Gently conditions skin for everyday use • Effective, yet gentle and mild, so it is great for the entire family • Contains moisturizer

Uses 50% less plastic per ounce vs. 7.5 fl oz pumps • Citrus scent

Active ingredient

Benzalkonium chloride 0.13%

Purpose

Antibacterial

Use

for handwashing to decrease bacteria on the skin

Warnings

For external use only: hands only

When using this product

- avoid contact with eyes. If contact occurs, rinse eyes thoroughly with water.

Stop use and ask a doctor if

- irritation and redness develop
- condition persists for more than 72 hours

Keep out of reach of children.

If swallowed, get medical help or contact a Poison Control Center right away.

Directions

- wet hands
- apply palmful to hands
- scrub thoroughly
- rinse thoroughly

Inactive ingredients

water, lauramine oxide, cocamidopropyl betaine, lauramidopropylamine oxide, sodium chloride, myristamidopropylamine oxide, glycerin, fragrance, disteareth-75 IPDI, PEG-150 distearate, citric acid, tetrasodium EDTA, benzophenone-4, sodium benzoate, red 33, red 40, yellow 5

ADVERSE REACTION

Distributed by: Wakerfern Food Corp.

5000 Riverside Drive, Keasbey, NJ 08832

Paperbird is trademarked by:

Wakefern Food Corp. ©2022

QUALITY ASSURED

1-800-ShopRite • 1-800-746-7748

www.shoprite.com

how2recycle.info

Empty Before Recycling

PLASTIC BOTTLE

principal display panel

A SHOPRITE®BRAND

paperbird™

fresh citrus scent

Antibacterial Liquid Hand Soap

QUALTIY ASSURED

light moisturizing antibacterial

Paraben-free • Phthalate-free

Dermatologist tested • Triclosan-free

NET 50 FL OZ (1 QT 1 PT 2 FL OZ) 1.47 L